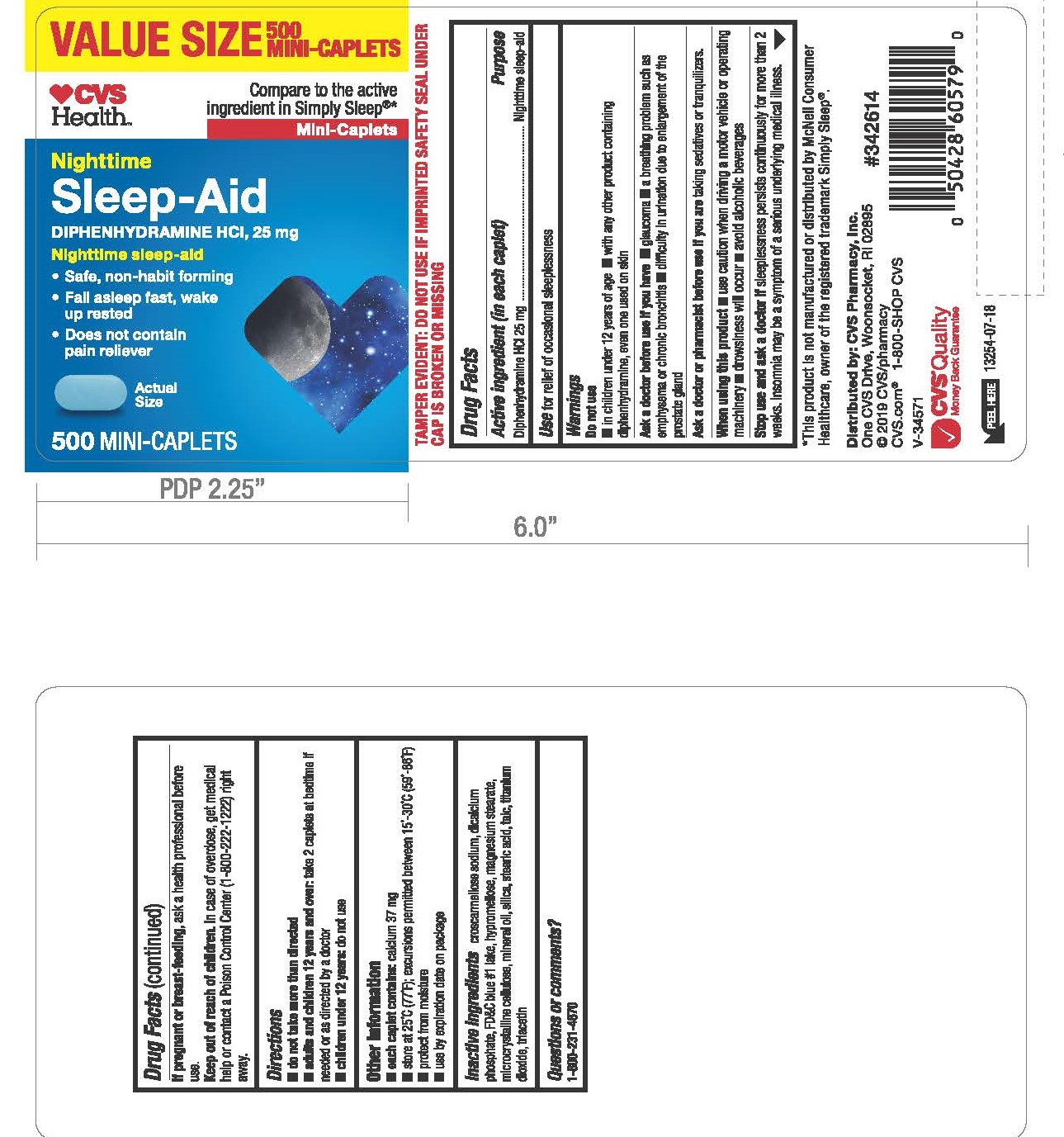 DRUG LABEL: DIPHENHYDRAMINE HYDROCHLORIDE
NDC: 69842-834 | Form: TABLET, FILM COATED
Manufacturer: CVS Pharmacy, Inc.
Category: otc | Type: HUMAN OTC DRUG LABEL
Date: 20241202

ACTIVE INGREDIENTS: DIPHENHYDRAMINE HYDROCHLORIDE 25 mg/1 1
INACTIVE INGREDIENTS: LIGHT MINERAL OIL; TITANIUM DIOXIDE; TRIACETIN; CALCIUM PHOSPHATE, DIBASIC, DIHYDRATE; FD&C BLUE NO. 1; MICROCRYSTALLINE CELLULOSE; SILICON DIOXIDE; STEARIC ACID; MAGNESIUM STEARATE; TALC; CROSCARMELLOSE SODIUM; HYPROMELLOSES

2834-CVS

Drug Facts

Active ingredient (in each caplet)

Diphenhydramine HCl 25 mg

Purpose

Nighttime sleep-aid

Use

for relief of occasional sleeplessness

Warnings

Do not use

■ in children under 12 years of age

■ with any other product containing diphenhydramine, even one used on skin

Ask a doctor before use if you have

■ glaucoma

■ a breathing problem such as emphysema or chronic bronchitis

■ difficulty in urination due to enlargement of the prostate gland

Ask a doctor or pharmacist before use if you are

taking sedatives or tranquilizers.

When using this product

■ use caution when driving a motor vehicle or operating machinery ■ drowsiness will occur

■ avoid alcoholic beverages

Stop use and ask a doctor if

sleeplessness persists continuously for more than 2 weeks. Insomnia may be a symptom of a serious underlying medical illness.

If pregnant or breast-feeding,

ask a health professional before use.

OVERDOSAGE

In case of overdose, get medical help or contact a Poison Control Center (1-800-222-1222) right away.

Directions

■ do not take more than directed

■ adults and children 12 years and over: take 2 caplets at bedtime if needed or as directed by a doctor

■ children under 12 years: do not use

Other information

■ each caplet contains: calcium 37 mg

■ store at 25°C (77°F); excursions permitted between 15°-30°C (59°-86°F)

■ protect from moisture

■ use by expiration date on package

Inactive ingredients

croscarmellose sodium, dicalcium phosphate, FD&C blue #1 lake, hypromellose, magnesium stearate, microcrystalline cellulose, mineral oil, silica, stearic acid, talc, titanium dioxide, triacetin

Questions or comments?

1-800-231-4670

TAMPER EVIDENT: DO NOT USE IF IMPRINTED SAFETY SEAL UNDER CAP IS BROKEN OR MISSING

*This product is not manufactured or distributed by McNeil Consumer Healthcare, owner of the registered trademark

Simply Sleep®.

Distributed by: CVS Pharmacy, Inc.

One CVS Drive, Woonsocket, RI 02895

© 2018 CVS/pharmacy

CVS.com® 1-800-SHOP CVS

V-34571

PACKAGE LABEL

CVSHealth

Compare to the active ingredient in Simply Sleep®*

Nighttime

Sleep-Aid

DIPHENHYDRAMINE HCl, 25 mg

Nighttime sleep-aid

• Safe, non-habit forming

• Fall asleep fast, wake up rested

• Does not contain pain reliever

500 MINI-CAPLETS